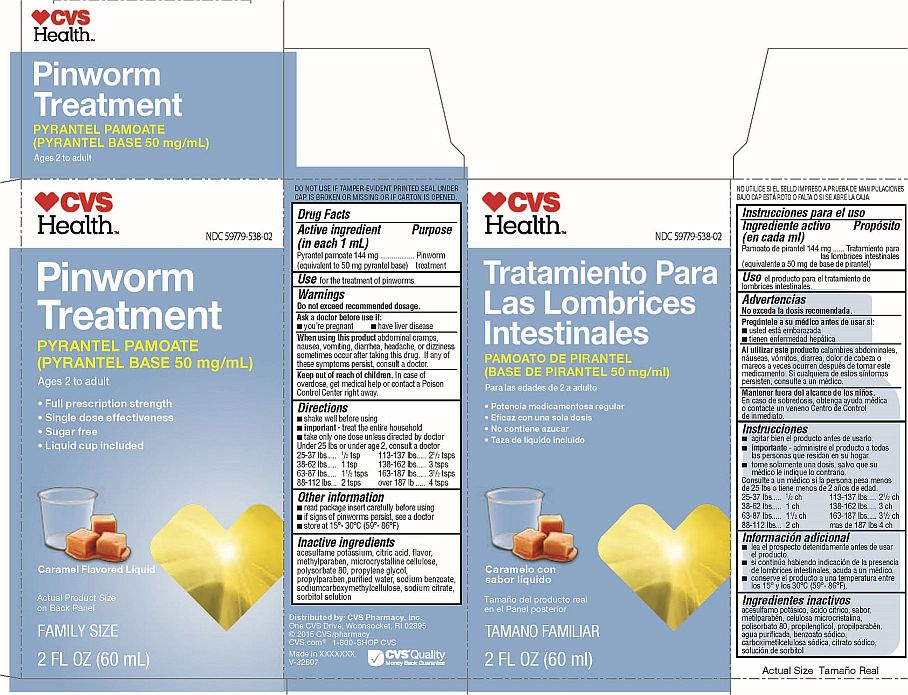 DRUG LABEL: Pinworm Treatment
NDC: 59779-538 | Form: SUSPENSION
Manufacturer: CVS Pharmacy Inc.
Category: otc | Type: HUMAN OTC DRUG LABEL
Date: 20150811

ACTIVE INGREDIENTS: PYRANTEL PAMOATE 144 mg/1 mL
INACTIVE INGREDIENTS: SODIUM BENZOATE; CARBOXYMETHYLCELLULOSE SODIUM; SODIUM CITRATE; SORBITOL; ACESULFAME POTASSIUM; CITRIC ACID MONOHYDRATE; METHYLPARABEN; CELLULOSE, MICROCRYSTALLINE; POLYSORBATE 80; PROPYLPARABEN; WATER; PROPYLENE GLYCOL

CVS Pinworm Treatment

Pinworm Treatment

NDC 59779-538-02

PYRANTEL PAMOATE

(PYRANTEL BASE 50 mg/mL)

Ages 2 to Adult

- Full prescription strength
- Single dose effectiveness
- Sugar free
- Liquid cup included

Caramel Flavored Liquid

Actual Product Size on Back Panel

FAMILY SIZE

2 FL OZ (60 mL)

DO NOT USE IF TAMPER-EVIDENT SEAL UNDER CAP IS BROKEN OR MISSING OR IF CARTON IS OPENED.

Active ingredient (in each 1 mL)

Pyrantel pamoate 144 mg

(equivalent to 50 mg pyrantel base)

Purpose

Pinworm treatment

Use

for the treatment of pinworms.

Warnings

Do not exceed recommended dosage.

Ask a doctor before use if:

- you're pregnant
- have liver disease

When using this product abdominal cramps, nausea, vomiting, diarrhea, headache, or dizziness sometimes occur after taking this drug. If any of these symptoms persist, consult a doctor.

Keep out of reach of children. In case of overdose, get medical help or contact a Poison Control Center right away.

Directions

- shake well before using
- important - treat the entire household
- take only one dose unless directed by a doctor

Under 25 lbs or under age 2, consult a doctor

25-37 lbs.....^1/2 tsp

36-62 lbs.....1 tsp

63-87 lbs.....1^1/2 tsps

88-112 lbs....2 tsps

113-137 lbs.....2^1/2 tsps

138-162 lbs.....3 tsps

163-187 lbs.....3^1/2 tsps

over 187 lbs.....4 tsps

Other information

- read package insert carefully before using
- if signs of pinworms persist, see a doctor

STORAGE AND HANDLING

- store at 15°-30°C (59°-86°F)

Inactive ingredients

acesulfame potassium, citric acid, flavor, methylparaben, microcrystalline cellulose, polysorbate 80, propylene glycol, propylparaben, purified water, sodium benzoate, sodiumcarboxymethylcellulose, sodium citrate, sorbitol solution

Distributed by: CVS Pharmacy, Inc.

One CVS Drive, Woonsocket, RI 02895

© 2015 CVS/pharmacy

CVS.com® 1-800-SHOP CVS

Made in XXXXXXX

V-32607

CVS Quality

Money Back Guarantee